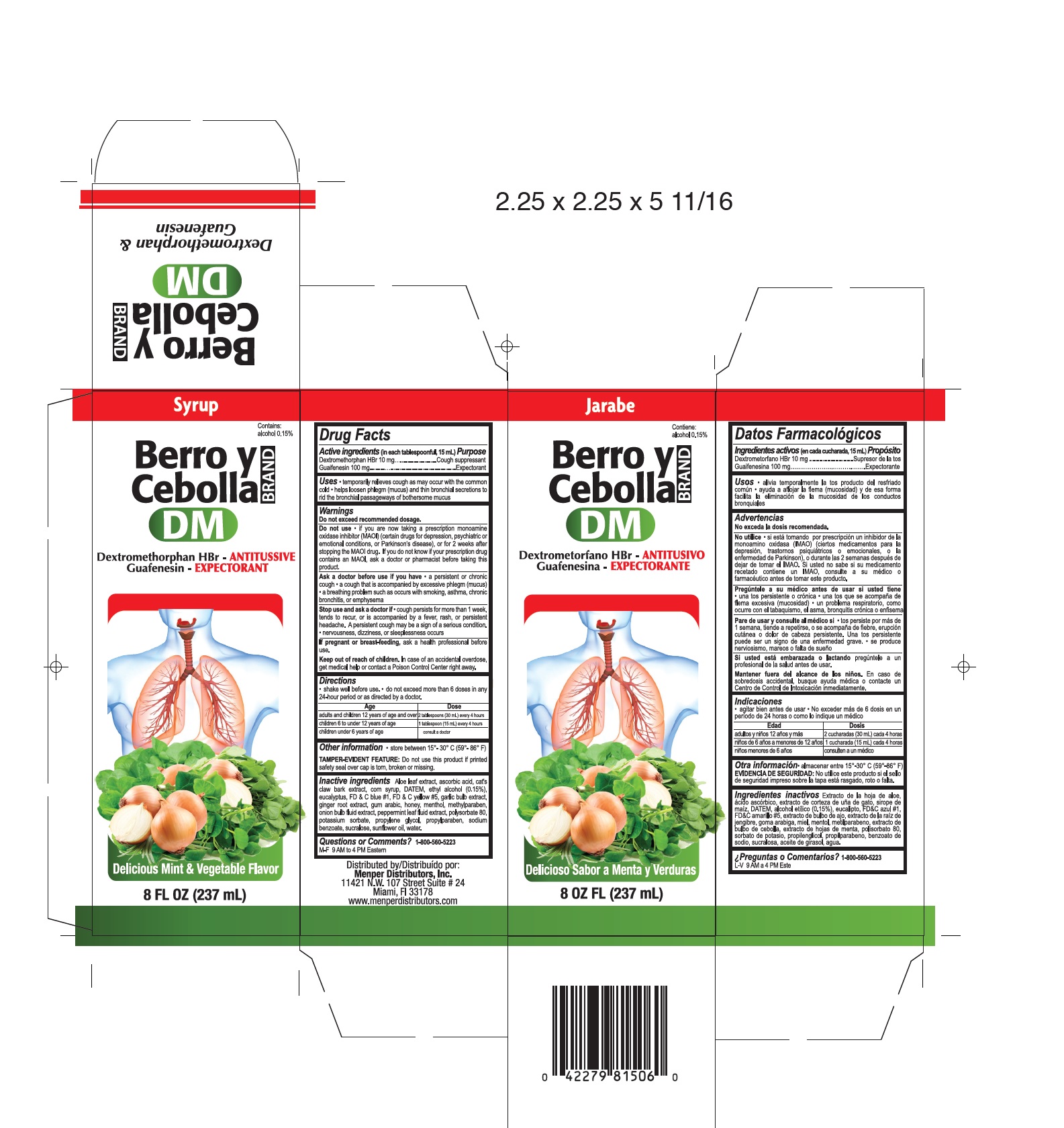 DRUG LABEL: Berro y Cebolla
NDC: 53145-080 | Form: LIQUID
Manufacturer: Menper Distributors, Inc.
Category: otc | Type: HUMAN OTC DRUG LABEL
Date: 20250722

ACTIVE INGREDIENTS: DEXTROMETHORPHAN HYDROBROMIDE 10 mg/15 mL; GUAIFENESIN 100 mg/15 mL
INACTIVE INGREDIENTS: ALOE; ASCORBIC ACID; CAT'S CLAW; CORN SYRUP; DIACETYLTARTARIC AND FATTY ACID ESTERS OF GLYCEROL; ALCOHOL; EUCALYPTUS ALBA LEAF; FD&C BLUE NO. 1; FD&C YELLOW NO. 5; GARLIC; GINGER; ACACIA; HONEY; MENTHOL; METHYLPARABEN; ONION; PEPPERMINT; POLYSORBATE 80; POTASSIUM SORBATE; PROPYLENE GLYCOL; PROPYLPARABEN; SODIUM BENZOATE; SUCRALOSE; SUNFLOWER OIL; WATER

Berro y Cebolla

Active Ingredients in each 15mL

Dextromethorphan HBr - 10mg

Guaifenesin - 100mg

Purpose

Cough Suppressant

Expectorant

Uses

- temporarily relieves cough as may occur with the common cold

- helps loosen phlegm (mucus) and thin bronchial secretions to rid the bronchial passageways of bothersome mucus

Do not exceed recommended dosage

Do not use

if you are now taking a prescription monamine oxidase inhibitor (MAOI) (certain drugs for depression, psychiatric or emotional conditions, or Parkinson's disease), or for 2 weeks after stopping the MAOI drug. If you do not know if your prescription drug contains an MAOI, ask a doctor or pharmacist before taking this product.

Ask a doctor before use if you have

a persistent or chronic cough
a cough that is accompanied by excessive phlegm (mucus)
a breathing problem such as occurs with smoking, asthma, chronic bronchitis, or emphysema

Stop use and ask a doctor if

- cough persists for more than 1 week, tends to recur, or is accompanied by a fever, rash, or persistent headache. A persistent cough may be a sign of a serious condition
- nervousness, dizziness, or sleeplessness occurs

If pregnant or breast-feeding

ask a health professional before use.

Keep out of reach of children.

In case of accidental overdose, get medical help or contact a Poison Control Center right away.

Directions

shake well before use
do not exceed more than 6 doses in any 24-hour period or as directed by a doctor.

AGE Dose
adults and children 12 years of age and over 2 tablespoons (30 mL) every 4 hours
children 6 to under 12 years of age 1 tablespoon (15 mL) every 4 hours
children under 6 years of age consult a doctor

Other information

store between 15° - 30° C (59° - 86° F)

Tamper-Evident Feature: Do not use this product if printed safety seal over cap is torn, broken or missing.

Inactive ingredients

Aloe leaf extract, ascorbic acid, cat's claw bark extract, corn syrup, DATEM, ethyl alcohol (0.15%), eucalyptus, FD&C blue #1, FD&C yellow #5, garlic bulb extract, ginger root extract, gum arabic, honey, menthol, methylparaben, onion bulb fluid extract, peppermint leaf fluid extract, polysorbate 80, potassium sorbate, propylene glycol, propylparaben, sodium benzoate, sucralose, sunflower oil, water.

Questions or Comments?

1-800-560-5223 M-F 9 AM to 4 PM Eastern